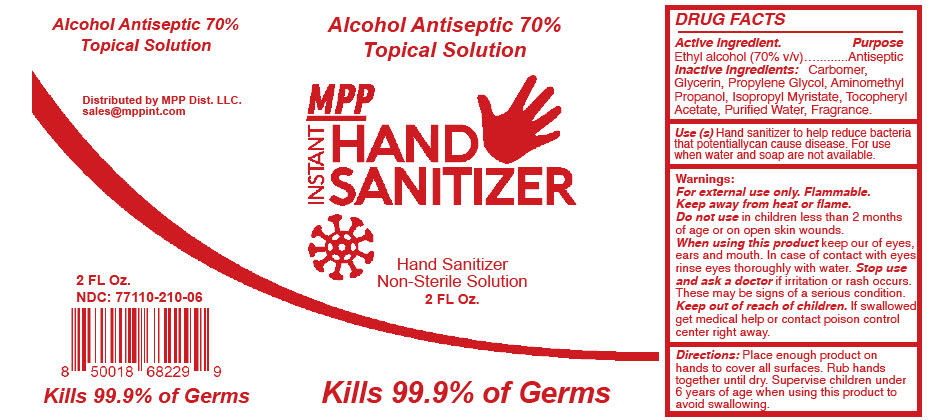 DRUG LABEL: Hand Sanitizer
NDC: 77110-210 | Form: SOLUTION
Manufacturer: Biominerales Pharma
Category: otc | Type: HUMAN OTC DRUG LABEL
Date: 20200727

ACTIVE INGREDIENTS: Alcohol 70 mL/100 mL
INACTIVE INGREDIENTS: Carbomer Homopolymer, unspecified type; Glycerin; Propylene Glycol; Aminomethylpropanol; Isopropyl Myristate; .Alpha.-Tocopherol Acetate; Water

HAND SANITIZER

DRUG FACTS

Active ingredient

Ethyl alcohol (70% v/v)

Purpose

Antiseptic

Inactive ingredients

Carbomer, Glycerin, Propylene Glycol, Aminomethyl Propanol, Isopropyl Myristate, Tocopheryl Acetate, Purified Water, Fragrance.

Use (s)

Hand sanitizer to help reduce bacteria that potentiallycan cause disease. For use when water and soap are not available.

Warnings

For external use only. Flammable.

Keep away from heat or flame.

Do not use in children less than 2 months of age or on open skin wounds.

When using this product keep our of eyes, ears and mouth. In case of contact with eyes, rinse eyes thoroughly with water. Stop use and ask a doctor if irritation or rash occurs. These may be signs of a serious condition.

Keep out of reach of children. If swallowed, get medical help or contact poison control center right away.

Directions

Place enough product on hands to cover all surfaces. Rub hands together until dry. Supervise children under 6 years of age when using this product to avoid swallowing.

Distributed by MPP Dist. LLC.

PRINCIPAL DISPLAY PANEL - 2 FL Oz. Bottle Label

Alcohol Antiseptic 70%
Topical Solution

MPP
INSTANT
HAND
SANITIZER

Hand Sanitizer
Non-Sterile Solution
2 FL Oz.

Kills 99.9% of Germs